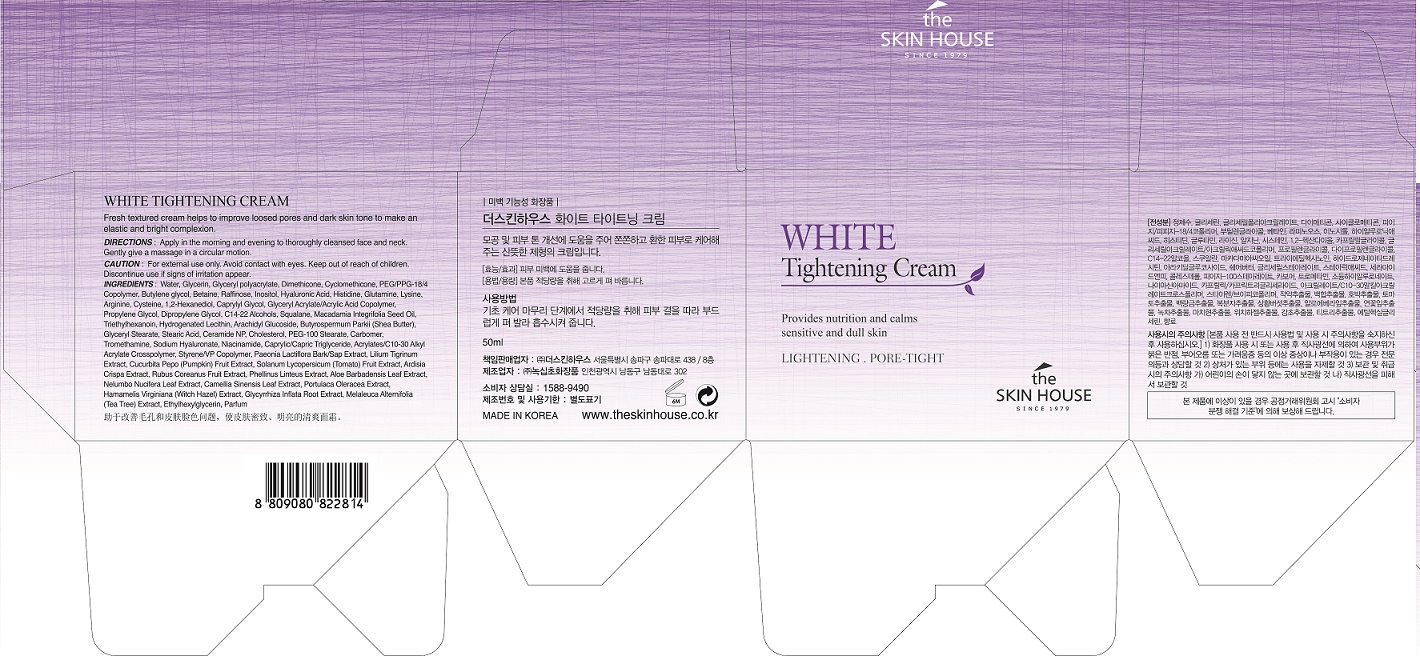 DRUG LABEL: THE SKINHOUSE WHITE TIGHTENINGCREAM
NDC: 73590-0001 | Form: CREAM
Manufacturer: NOKSIBCHO cosmetic Co., Ltd.
Category: otc | Type: HUMAN OTC DRUG LABEL
Date: 20200127

ACTIVE INGREDIENTS: NIACINAMIDE 2 g/100 mL
INACTIVE INGREDIENTS: WATER; BUTYLENE GLYCOL

Drug Facts

ACTIVE INGREDIENT

Niacinamide, HamamelisVirginiana (Witch Hazel) Extract, PaeoniaLactiflora Bark/ Sap Extract, LiliumTigrinum Extract, ArdisiaCrispa Extract, Phellinus Linteus Extract, Camellia Sinensis Leaf Extract

INACTIVE INGREDIENT

Glycerin
Glyceryl polyacrylate
PEG/PPG-18/4 Copolymer
Water
Butylene glycol
Betaine
Raffinose
Inositol
Hyaluronic Acid
Histidine
Glutamine
Glycerin
Lysine
Arginine
Cysteine
1,2-Hexanediol
Caprylyl Glycol
Glycerin
Glyceryl Acrylate/Acrylic Acid Copolymer
Propylene Glycol
Dipropylene Glycol
Dimethicone
Water
Glycerin
C14-22 Alcohols
Squalane
Macadamia Integrifolia Seed Oil
Triethylhexanoin
Hydrogenated Lecithin
Arachidyl Glucoside
Butyrospermum Parkii (Shea Butter)
1,2-Hexanediol
Glyceryl Stearate
Stearic Acid
Ceramide NP
Cholesterol
PEG-100 Stearate
Dimethicone
Carbomer
Tromethamine
Sodium Hyaluronate
Niacinamide
1,2-Hexanediol
Glycerin
Glyceryl Acrylate/Acrylic Acid Copolymer Propylene Glycol
Butylene glycol
Glycerin
Caprylic/Capric Triglyceride
Water
Hydrogenated Lecithin
1,2-Hexanediol
Ceramide NP
Arginine
Acrylates/C10-30 Alkyl Acrylate Crosspolymer
Cyclomethicone
Styrene/VP Copolymer
Paeonia Lactiflora Bark/Sap Extract
Lilium Tigrinum Extract
Cucurbita Pepo (Pumpkin) Fruit Extract
Solanum Lycopersicum (Tomato) Fruit Extract
Ardisia Crispa Extract
Rubus Coreanus Fruit Extract
Phellinus Linteus Extract
Aloe Barbadensis Leaf Extract
Nelumbo Nucifera Leaf Extract
Camellia Sinensis Leaf Extract
Portulaca Oleracea Extract
Hamamelis Virginiana (Witch Hazel) Extract
Glycyrrhiza Inflata Root Extract
Melaleuca Alternifolia (Tea Tree) Extract
Ethylhexylglycerin
Parfum

PURPOSE

For those who want whitening products but not dry one.

If you still feel like you need more moisture when you finish up to emulsion step, you can use the cream for moisture supply. It controls and balances the oil and moisture level and supply moisture to skin. Besides, it also tightens the pore to make the skin texture smooth. And brightens the skin tone to become ceramic skin. Once you apply the cream to skin, it will be absorbed to skin immediately and give you fresh feeling.

keep out of reach of the children

INDICATIONS AND USAGE

After cleansing, use toner to smooth the skin texture.

Apply the serum or the emulsion to the face, and let it be absorbed deeply into skin.

Apply a small amount of the cream to the face, and spread it along the skin texture.

WARNINGS

For external use only
When using this product

■ if the following symptoms occurs after use, stop use and consult with a skin specialist

red specks, swelling, itching

■ don’t use on the part where there is injury, eczema, or dermatitis

Keep out of reach of children

■ if swallowed, get medical help or contact a person control center immediately

DOSAGE AND ADMINISTRATION

for external use only